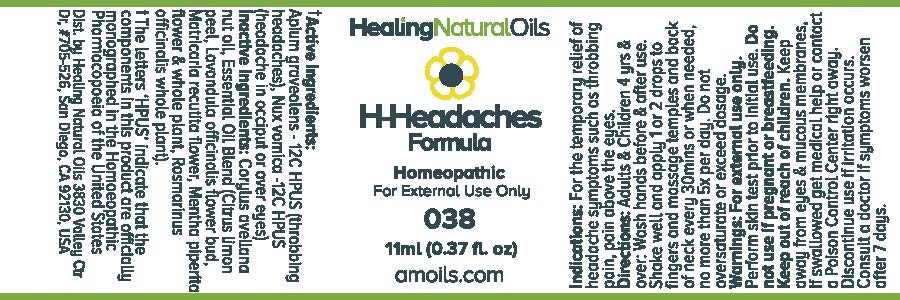 DRUG LABEL: H-Headaches Formula
NDC: 61077-038 | Form: OIL
Manufacturer: Healing Natural Oils LLC
Category: homeopathic | Type: HUMAN OTC DRUG LABEL
Date: 20171227

ACTIVE INGREDIENTS: CELERY SEED 12 [hp_C]/11 mL; STRYCHNOS NUX-VOMICA SEED 12 [hp_C]/11 mL
INACTIVE INGREDIENTS: EUROPEAN HAZELNUT OIL; LEMON PEEL; LAVANDULA ANGUSTIFOLIA FLOWER; CHAMOMILE; PEPPERMINT; ROSMARINUS OFFICINALIS WHOLE

Active Ingredients:

Apium graveolens - 12C HPUS
Nux vomica -12C HPUS

Purpose

Apium graveolens - 12C HPUS (throbbing headaches),
Nux vomica -12C HPUS (headache in occiput or over eyes)
The letters ‘HPUS’ indicate that the components in this product are officially
monographed in the Homoeopathic Pharmacopoeia of the United States

Inactive Ingredients:

Corylus avellana nut oil, Essential Oil Blend (Citrus limon peel,
Lavandula officinalis flower bud, Matricaria
recutita flower, Mentha piperita flower and
whole plant, Rosmarinus officinalis whole
plant).

Indications:

For the temporary relief of headache symptoms such as throbbing pain, pain above the eyes.

Directions:

Adults and Children 4 yrs and over: Wash hands before and after use.
Shake well and apply 1 or 2 drops to fingers and massage temples and back of neck every 30mins or when needed, no more than 5x per day.
Do not oversaturate or exceed dosage.

Warnings:

For external use only.
Perform skin test prior to initial use.

Do not use if pregnant or breastfeeding.

Keep out of reach of children.

OTHER SAFETY INFORMATION

Keep away from eyes and mucous membranes. If swallowed get medical help or contact a Poison Control
Center right away.

Discontinue use if irritation occurs.

ASK DOCTOR

Consult a doctor if symptoms worsen after 7 days.

DESCRIPTION

Dist. by Healing Natural Oils 3830 Valley Ctr Dr, #705-526, San Diego, CA 92130, USA

PACKAGE LABEL

Healing Natural Oils

H-Headaches

Formula

Homeopathic

For External Use Only

038

11ml (0.37 fl. oz)
amoils.com